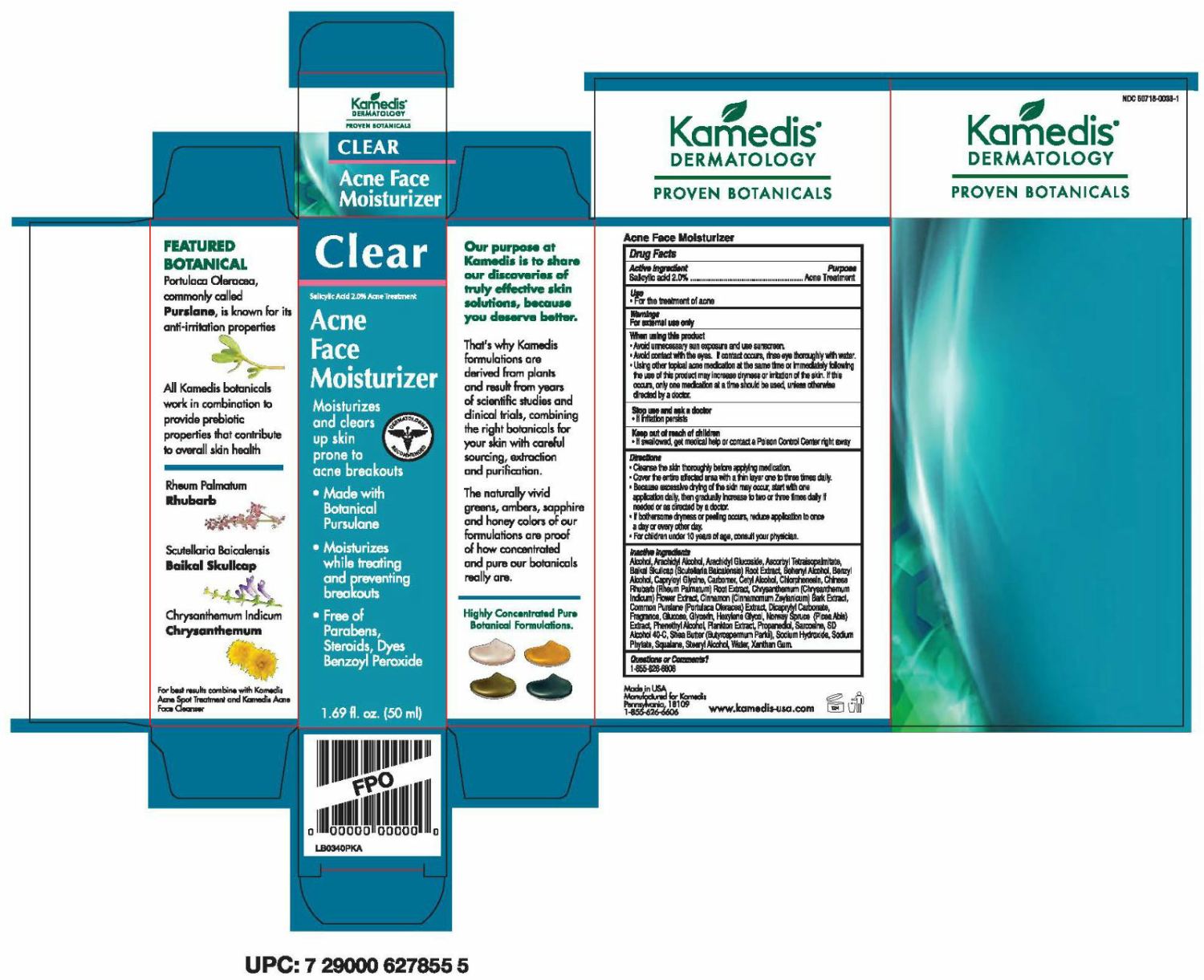 DRUG LABEL: Clear Acne Face Moisturizer
NDC: 50718-0033 | Form: LOTION
Manufacturer: Kamedis
Category: otc | Type: HUMAN OTC DRUG LABEL
Date: 20240207

ACTIVE INGREDIENTS: SALICYLIC ACID 28.8 mg/1 mL
INACTIVE INGREDIENTS: ARACHIDYL ALCOHOL; ALCOHOL; ARACHIDYL GLUCOSIDE; ASCORBYL TETRAISOPALMITATE; SCUTELLARIA BAICALENSIS ROOT; BENZYL ALCOHOL; CAPRYLOYL GLYCINE; CETYL ALCOHOL; PURSLANE; CHLORPHENESIN; RHEUM PALMATUM ROOT; CHRYSANTHEMUM INDICUM FLOWER; DICAPRYLYL CARBONATE; GLYCERIN; HEXYLENE GLYCOL; PICEA ABIES WOOD; PROPANEDIOL; SARCOSINE; WATER; XANTHAN GUM; CINNAMON BARK OIL; SHEA BUTTER; SODIUM HYDROXIDE; PHYTATE SODIUM; SQUALANE; STEARYL ALCOHOL; DOCOSANOL; PHENYLETHYL ALCOHOL; DEXTROSE, UNSPECIFIED FORM; CARBOMER INTERPOLYMER TYPE A (ALLYL SUCROSE CROSSLINKED); NORI

Clear Acne Face Moisturizer

Drug Facts

Active Ingredient

Salicylic acid 2.0%

Purpose

Acne Treatment

Use

- For the treatment of acne

Warnings

For external use only

When using this product

- Avoid unnecessary sun exposure and use
  sunscreen.
- Avoid contact with the eyes. If contact occurs, rinse eyes thoroughly with water.
- Using other topical acne medication at the same time or immediately following the use of this product may increase dryness or irritation of the skin. If this occurs, only one medication at a time should be used, unless otherwise directed by a doctor.

Stop use and ask a doctor

- If irritation persists

Keep out of reach of children

- If swallowed, get medical help or contact a Poison Control Center right away.

Directions

- Cleanse the skin thoroughly before applying medication.
- Cover the entire affected area with a thin layer one to three times daily.
- Because excessive drying of the skin may occur, start with one application daily, then gradually increase to two or three times daily if needed or as directed by a doctor.
- If bothersome dryness or peeling occurs, reduce application to once a day or every other day.
- For children under 10 years of age, consult your physician.

Inactive Ingredients

Alcohol, Arachidyl Alcohol, Arachidyl Glucoside, Ascorbyl Tetraisopalmitate, Baikal Skullcap (Scutellaria Baicalensis) Root Extract, Behenyl Alcohol, Benzyl Alcohol, Capryloyl Glycine, Carbomer, Cetyl Alcohol, Chlorphenesin, Chinese Rhubarb (Rheum Palmatum) Root Extract, Chrysanthemum (Chrysanthemum Indicum) Flower Extract, Cinnamon (Cinnamomum Zeylanicum) Bark Extract, Common Purslane (Portulaca Oleracea) Extract, Dicaprylyl Carbonate, Fragrance, Glucose, Glycerin, Hexylene Glycol, Norway Spruce (Picea Abis) Extract, Phenethyl Alcohol, Plankton Extract, Propanediol, Sarcosine, SD Alcohol 40-C, Shea Butter (Butyrospermum Parkii), Sodium Hydroxide, Sodium Phytate, Squalane, Stearyl Alcohol, Water, Xanthan Gum.

Questions or Comments?

1-855-626-6606

Made in USA
Manufactured for Kamedis
Pennsylvania, 18109
1-855-626-6606

www.kamedis-usa.com